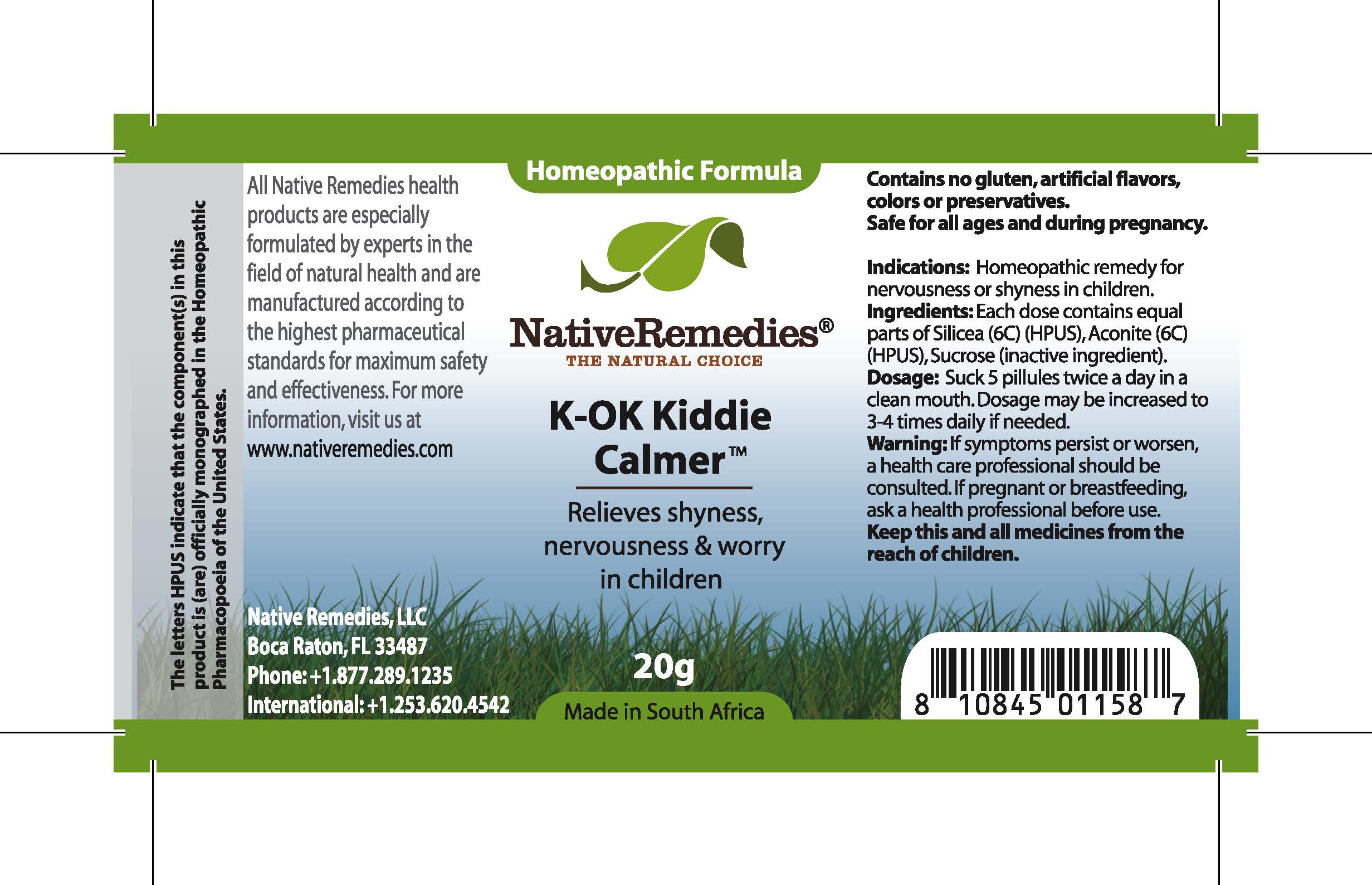 DRUG LABEL: K-OK Kiddie Calmer 
NDC: 68647-102 | Form: TABLET
Manufacturer: Feelgood Health
Category: homeopathic | Type: HUMAN OTC DRUG LABEL
Date: 20100715

ACTIVE INGREDIENTS: SILICON DIOXIDE 6 [hp_C]/1 1; ACONITUM NAPELLUS 6 [hp_C]/1 1
INACTIVE INGREDIENTS: SUCROSE

KOK KIDDIE CALMER

DESCRIPTION

Relieves shyness, nervousness and worry in children

INDICATIONS AND USAGE

Indications: Homeopathic remedy for nervousness or shyness in children.

DOSAGE AND ADMINISTRATION

Dosage: Dissolve 5 pilules twice a day in a clean mouth. Dosage may be increased to 3-4 times daily if needed.

GENERAL PRECAUTIONS

Caution: If symptoms persist or worsen, a health care professional should be consulted. Keep this and all medicines from the reach of children.

ACTIVE INGREDIENT

Ingredients: Each dose contains equal parts of Silicea (6C) (HPUS), Aconite (6C) (HPUS)

Sucrose inactive ingredient)

PREGNANCY

If pregnant or breastfeeding, ask a health professional before use.

USER SAFETY WARNINGS

Contains no gluten, artificial flavors, colors or preservatives.Safe for all ages and during pregnancy.

PATIENT COUNSELING INFORMATION

All Native Remedies health products are especially formulated by experts in the field of natural health and are manufactured according to the highest pharmaceutical standards for maximum safety and effectiveness. For more information, visit us at www.nativeremedies.com

Distributed by

Native Remedies, LLC

6531 Park of Commerce Blvd.

Suite 160

Boca Raton, FL 33487

Phone: +1.877.289.1235

International: +1.561.999.8857

The letters HPUS indicate that the component(s) in this product is (are) officially monographed in the Homeopathic Pharmacopoeia of the United States.